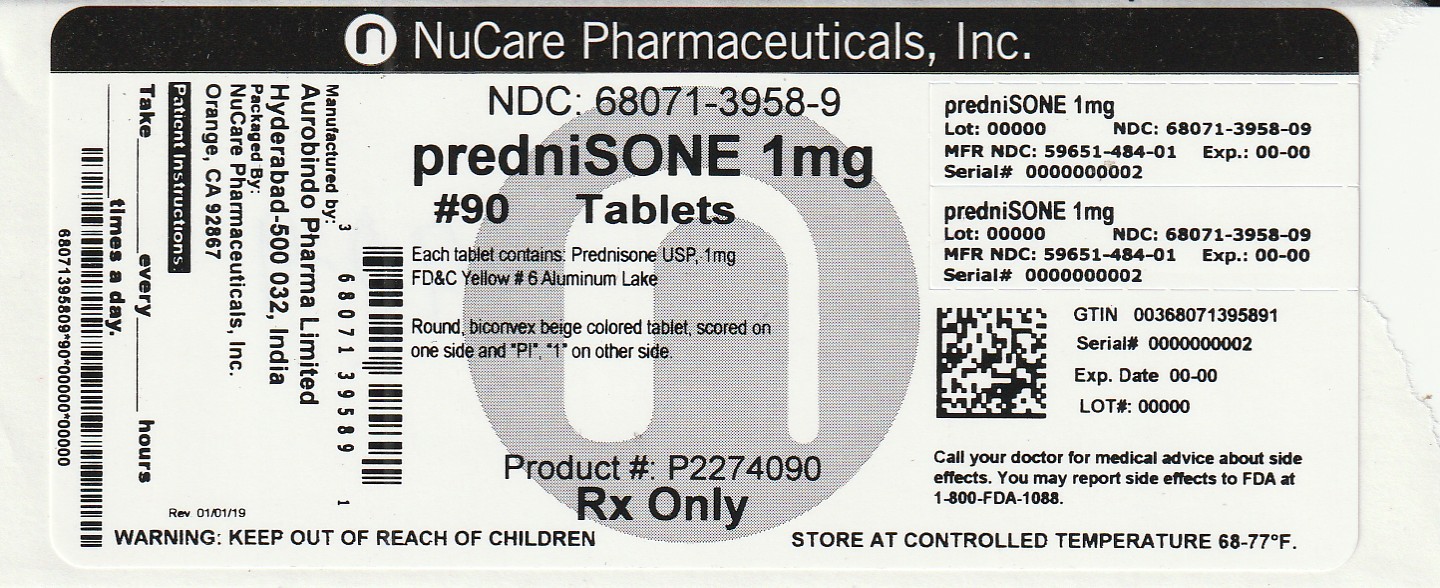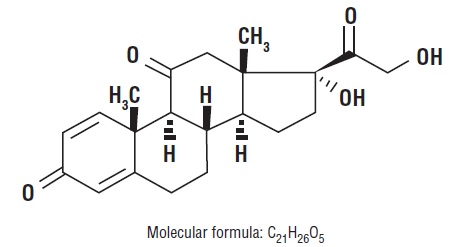 DRUG LABEL: PREDNISONE
NDC: 68071-3958 | Form: TABLET
Manufacturer: NuCare Pharmaceuticals, Inc.
Category: prescription | Type: HUMAN PRESCRIPTION DRUG LABEL
Date: 20260126

ACTIVE INGREDIENTS: PREDNISONE 1 mg/1 1
INACTIVE INGREDIENTS: D&C YELLOW NO. 10 ALUMINUM LAKE; FD&C YELLOW NO. 6; LACTOSE MONOHYDRATE; MAGNESIUM STEARATE; MICROCRYSTALLINE CELLULOSE 101; STARCH, CORN; SODIUM STARCH GLYCOLATE TYPE A

Prednisone Tablets, USP
Rx only

DESCRIPTION

Glucocorticoids are adrenocortical steroids, both naturally occurring and synthetic, that are readily absorbed from the gastrointestinal tract. The formula for prednisone is C21H26O5. Chemically, it is 17,21-dihydroxypregna-1,4-diene-3,11,20-trione and has the following structure.:

Prednisone USP is a white to partially white, odorless, crystalline powder and has a molecular weight of 358.43. It melts at about 230°C with some decomposition.

Prednisone USP is very slightly soluble in water; slightly soluble in alcohol, chloroform, dioxane, and methanol. Prednisone tablets USP contain 1 mg prednisone, USP.

The inactive ingredients for prednisone tablets USP include: D&C yellow No.10 aluminum lake, FD&C yellow # 6 aluminum lake, lactose monohydrate, magnesium stearate, microcrystalline cellulose, pregelatinized starch (maize), and sodium starch glycolate.

Meets USP Dissolution Test 2.

ACTIONS

Naturally occurring glucocorticoids (hydrocortisone and cortisone), which also have salt-retaining properties, are used as replacement therapy in adrenocortical deficiency states. Their synthetic analogs, such as prednisone, are primarily used for their potent anti-inflammatory effects in disorders of many organ systems. Glucocorticoids, such as prednisone, cause profound and varied metabolic effects. In addition, they modify the body's immune response to diverse stimuli.

INDICATIONS

Endocrine disorders:primary or secondary adrenocortical insufficiency (hydrocortisone or cortisone is the first choice; synthetic analogs may be used in conjunction with mineralocorticoids where applicable; in infancy mineralocorticoid supplementation is of particular importance), congenital adrenal hyperplasia, nonsuppurative thyroiditis, hypercalcemia associated with cancer.

Rheumatic disorders: as adjunctive therapy for short-term administration (to tide the patient over an acute episode or exacerbation) in: psoriatic arthritis; rheumatoid arthritis, including juvenile rheumatoid arthritis (selected cases may require low-dose maintenance therapy); ankylosing spondylitis; acute and subacute bursitis; acute nonspecific tenosynovitis; acute gouty arthritis; posttraumatic osteoarthritis; synovitis of osteoarthritis; epicondylitis.

Collagen diseases: during an exacerbation or as maintenance therapy in selected cases of systemic lupus erythematosus, acute rheumatic carditis.

Dermatologic diseases: pemphigus, bullous dermatitis herpetiformis, severe erythema multiforme (Stevens-Johnson syndrome), exfoliative dermatitis, mycosis fungoides, severe psoriasis, severe seborrheic dermatitis.

Allergic states: control of severe or incapacitating allergic conditions intractable to adequate trials of conventional treatment: seasonal or perennial allergic rhinitis, serum sickness, bronchial asthma, contact dermatitis, atopic dermatitis, drug hypersensitivity reactions.

Ophthalmic diseases: severe acute and chronic allergic and inflammatory processes involving the eye and its adnexa, such as: allergic conjunctivitis, keratitis, allergic corneal marginal ulcers, herpes zoster ophthalmicus, iritis and iridocyclitis, chorioretinitis, anterior segment inflammation, diffuse posterior uveitis and choroiditis, optic neuritis, sympathetic ophthalmia.

Respiratory diseases:symptomatic sarcoidosis, Loeffler's syndrome not manageable by other means, berylliosis, fulminating or disseminated pulmonary tuberculosis when used concurrently with appropriate antituberculous chemotherapy, aspiration pneumonitis.

Hematologic disorders:idiopathic thrombocytopenic purpura in adults, secondary thrombocytopenia in adults, acquired (autoimmune) hemolytic anemia, erythroblastopenia (RBC anemia), congenital (erythroid) hypoplastic anemia.

Neoplastic Diseases

For palliative management of: leukemias and lymphomas in adults, acute leukemia of childhood.

Edematous states: to induce a diuresis or remission of proteinuria in the nephrotic syndrome, without uremia, of the idiopathic type or that due to lupus erythematosus.
Gastrointestinal diseases : to tide the patient over a critical period of the disease in ulcerative colitis, regional enteritis.

Miscellaneous:tuberculous meningitis with subarachnoid block or impending block when used concurrently with appropriate anti-tuberculous chemotherapy, trichinosis with neurologic or myocardial involvement.

In addition to the above indications, prednisone tablets are indicated for systemic dermatomyositis (polymyositis).

CONTRAINDICATIONS

CONTRAINDICATIONS:Prednisone tablets are contraindicated in systemic fungal infections.

WARNINGS

WARNINGS:In patients on corticosteroid therapy subject to any unusual stress, increased dosage of rapidly acting corticosteroids before, during and after the stressful situation is indicated.

Immunosuppression and Increased Risk of Infection

Corticosteroids, including prednisone, suppress the immune system and increase the risk of infection with any pathogen, including viral, bacterial, fungal, protozoan, or helminthic pathogens. Corticosteroids can:

- Reduce resistance to new infections
- Exacerbate existing infections
- Increase the risk of disseminated infections
- Increase the risk of reactivation or exacerbation of latent infections
- Mask some signs of infection

Corticosteroid-associated infections can be mild but can be severe and at times fatal. The rate of infectious complications increases with increasing corticosteroid dosages.

Monitor for the development of infection and consider prednisone withdrawal or dosage reduction as needed.

Tuberculosis

If prednisone is used to treat a condition in patients with latent tuberculosis or tuberculin reactivity, reactivation of tuberculosis may occur. Closely monitor such patients for reactivation. During prolonged prednisone therapy, patients with latent tuberculosis or tuberculin reactivity should receive chemoprophylaxis.

Varicella Zoster and Measles Viral Infections

Varicella and measles can have a serious or even fatal course in non-immune patients taking corticosteroids, including prednisone. In corticosteroid-treated patients who have not had these diseases or are non-immune, particular care should be taken to avoid exposure to varicella and measles:

- If a prednisone-treated patient is exposed to varicella, prophylaxis with varicella zoster immune globulin may be indicated. If varicella develops, treatment with antiviral agents may be considered.
- If a prednisone-treated patient is exposed to measles, prophylaxis with immunoglobulin may be indicated.

Hepatitis B Virus Reactivation

Hepatitis B virus reactivation can occur in patients who are hepatitis B carriers treated with immunosuppressive dosages of corticosteroids, including prednisone. Reactivation can also occur infrequently in corticosteroid-treated patients who appear to have resolved hepatitis B infection.

Screen patients for hepatitis B infection before initiating immunosuppressive (e.g., prolonged) treatment with prednisone. For patients who show evidence of hepatitis B infection, recommend consultation with physicians with expertise in managing hepatitis B regarding monitoring and consideration for hepatitis B antiviral therapy.

Fungal Infections

Corticosteroids, including prednisone, may exacerbate systemic fungal infections; therefore, avoid prednisone use in the presence of such infections unless prednisone is needed to control drug reactions. For patients on chronic prednisone therapy who develop systemic fungal infections, prednisone withdrawal or dosage reduction is recommended.

Amebiasis

Corticosteroids, including prednisone, may activate latent amebiasis. Therefore, it is recommended that latent amebiasis or active amebiasis be ruled out before initiating prednisone in patients who have spent time in the tropics or patients with unexplained diarrhea.

Strongyloides Infestation

Corticosteroids, including prednisone, should be used with great care in patients with known or suspected Strongyloides (threadworm) infestation. In such patients, corticosteroid-induced immunosuppression may lead to Strongyloides hyperinfection and dissemination with widespread larval migration, often accompanied by severe enterocolitis and potentially fatal gram-negative septicemia.

Cerebral Malaria

Avoid corticosteroids, including prednisone, in patients with cerebral malaria.

Kaposi’s Sarcoma

Kaposi’s sarcoma has been reported to occur in patients receiving corticosteroid therapy, most often for chronic conditions. Discontinuation of corticosteroids may result in clinical improvement of Kaposi’s sarcoma.

Prolonged use of corticosteroids may produce posterior subcapsular cataracts, glaucoma with possible damage to the optic nerves, and may enhance the establishment of secondary ocular infections due to fungi or viruses.

Usage in pregnancy: Since adequate human reproduction studies have not been done with corticosteroids, the use of these drugs in pregnancy, nursing mothers or women of childbearing potential requires that the possible benefits of the drug be weighed against the potential hazards to the mother and embryo or fetus. Infants born of mothers who have received substantial doses of corticosteroids during pregnancy should be carefully observed for signs of hypoadrenalism.

Average and large doses of hydrocortisone or cortisone can cause elevation of blood pressure, salt and water retention, and increased excretion of potassium. These effects are less likely to occur with the synthetic derivatives except when used in large doses. Dietary salt restriction and potassium supplementation may be necessary. All corticosteroids increase calcium excretion.

While on corticosteroid therapy patients should not be vaccinated against smallpox. Other immunization procedures should not be undertaken in patients who are on corticosteroids, especially on high doses, because of possible hazards of neurological complications and a lack of antibody response.

PRECAUTIONS

PRECAUTIONS: Information for Patients:Persons who are on immunosuppressant doses of corticosteroids should be warned to avoid exposure to chickenpox or measles. Patients should also be advised that if they are exposed, medical advice should be sought without delay.

GENERAL PRECAUTIONS

General:Drug-induced, secondary adrenocortical insufficiency may be minimized by gradual reduction of dosage. This type of relative insufficiency may persist for months after discontinuation of therapy; therefore, in any situation of stress occurring during that period, hormone therapy should be reinstituted. Since mineralocorticoid secretion may be impaired, salt and/or a mineralocorticoid should be administered concurrently.

There is an enhanced effect of corticosteroids in patients with hypothyroidism as in those with cirrhosis.

Corticosteroids should be used cautiously in patients with ocular herpes simplex because of possible corneal perforation.

The lowest possible dose of corticosteroid should be used to control the condition under treatment, and when reduction in dosage is possible, the reduction should be gradual.

Psychic derangements may appear when corticosteroids are used, ranging from euphoria, insomnia, mood swings, personality changes, and severe depression to frank psychotic manifestations. Also, existing emotional instability or psychotic tendencies may be aggravated by corticosteroids.

Aspirin should be used cautiously in conjunction with corticosteroids in hypoprothrombinemia.

Steroids should be used with caution in nonspecific ulcerative colitis, if there is a probability of impending perforation, abscess or other pyogenic infection; diverticulitis; fresh intestinal anastomoses; active or latent peptic ulcer; renal insufficiency; hypertension; osteoporosis; and myasthenia gravis.

Growth and development of infants and children on prolonged corticosteroid therapy should be carefully observed.

ADVERSE REACTIONS

Fluid and electrolyte disturbances:sodium retention, fluid retention, congestive heart failure in susceptible patients, potassium loss, hypokalemic alkalosis, hypertension.

Musculoskeletal:muscle weakness, steroid myopathy, loss of muscle mass, osteoporosis, vertebral compression fractures, aseptic necrosis of femoral and humeral heads, pathologic fracture of long bones.

Gastrointestinal:peptic ulcer with possible perforation and hemorrhage, pancreatitis, abdominal distention, ulcerative esophagitis.

Dermatologic:impaired wound healing, thin fragile skin, petechiae and ecchymoses, facial erythema, increased sweating, may suppress reactions to skin tests.

Neurological:convulsions, increased intracranial pressure with papilledema (pseudotumor cerebri) usually after treatment, vertigo, headache.

Endocrine:menstrual irregularities ; development of cushingoid state; suppression of growth in children; secondary adrenocortical and pituitary unresponsiveness, particularly in times of stress, as in trauma, surgery or illness; decreased carbohydrate tolerance; manifestations of latent diabetes mellitus; increased requirements of insulin or oral hypoglycemic agents in diabetics.

Ophthalmic:posterior subcapsular cataracts, increased intraocular pressure, glaucoma, exophthalmos.

Metabolic:negative nitrogen balance due to protein catabolism.

DOSAGE AND ADMINISTRATION:Dosage of prednisone tablets should be individualized according to the severity of the disease and the response of the patient. For infants and children, the recommended dosage should be governed by the same considerations rather than strict adherence to the ratio indicated by age or body weight.

Hormone therapy is an adjunct to, and not a replacement for, conventional therapy.

Dosage should be decreased or discontinued gradually when the drug has been administered for more than a few days.

The severity, prognosis, expected duration of the disease, and the reaction of the patient to medication are primary factors in determining dosage. If a period of spontaneous remission occurs in a chronic condition, treatment should be discontinued.

Blood pressure, body weight, routine laboratory studies, including two-hour postprandial blood glucose and serum potassium, and a chest X-ray should be obtained at regular intervals during prolonged therapy. Upper GI X-rays are desirable in patients with known or suspected peptic ulcer disease

The initial dosage of prednisone may vary from 5 mg to 60 mg per day, depending on the specific disease entity being treated. In situations of less severity lower doses will generally suffice, while in selected patients higher initial doses may be required. The initial dosage should be maintained or adjusted until a satisfactory response is noted. If after a reasonable period of time there is a lack of satisfactory clinical response, prednisone should be discontinued, and the patient transferred to other appropriate therapy. IT SHOULD BEEMPHASIZED THAT DOSAGE REQUIREMENTS ARE VARIABLE AND MUST BE INDIVIDUALIZED ON THE BASIS OF THE DISEASE UNDER TREATMENT AND THE RESPONSE OF THE PATIENT. After a favorable response is noted, the proper maintenance dosage should be determined by decreasing the initial drug dosage in small decrements at appropriate time intervals until the lowest dosage which will maintain an adequate clinical response is reached. It should be kept in mind that constant monitoring is needed in regard to drug dosage. Included in the situations which may make dosage adjustments necessary are changes in clinical status secondary to remissions or exacerbations in the disease process, the patient's individual drug responsiveness, and the effect of patient exposure to stressful situations not directly related to the disease entity under treatment; in this latter situation it may be necessary to increase the dosage of prednisone for period of time consistent with the patient's condition. If after long-term therapy the drug is to be stopped, it is recommended that it be withdrawn gradually rather than abruptly.

HOW SUPPLIED

Prednisone Tablets USP, 1 mgare beige colored, round, biconvex tablets, scored on one side and “PI”, “1” on other side. They are supplied as follows:

Bottles of 90 NDC 68071-3958-9
Store at20° to 25°C (68° to 77°F) [see USP Controlled Room Temperature].

Dispense in a tight, child-resistant container as defined in the USP/NF.

PROTECT FROM MOISTURE.
Distributed by:
Aurobindo Pharma USA, Inc.
279 Princeton-Hightstown Road
East Windsor, NJ 08520
Manufactured by:
Aurobindo Pharma Limited
Hyderabad-500 032, India
Revised: 02/2024